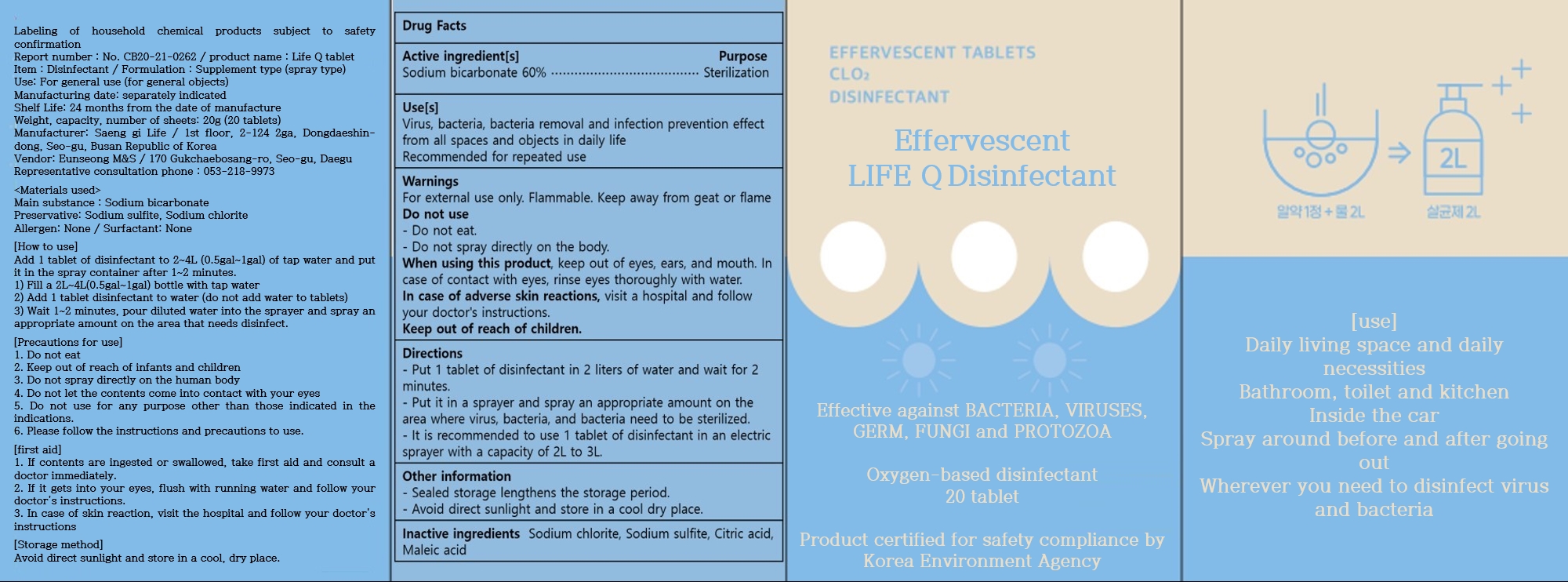 DRUG LABEL: LIFE Q
NDC: 80760-201 | Form: TABLET
Manufacturer: Saenggi Life
Category: otc | Type: HUMAN OTC DRUG LABEL
Date: 20211102

ACTIVE INGREDIENTS: SODIUM BICARBONATE 60 g/100 g
INACTIVE INGREDIENTS: SODIUM CHLORITE; SODIUM SULFITE; MALEIC ACID; CITRIC ACID MONOHYDRATE

80760-201

Active ingredient[s]

Sodium bicarbonate 60%

Purpose

Hand Sanitizer

Use[s]

Virus, bacteria, bacteria removal and infection prevention effect from all spaces and objects in daily life.

Recommended for repeated use.

Warinings

For external use only. Flammable. Keep away from geat or flame

Do not use

- Do not eat.
- Do not spray directly on the body.

When using this product

keep out of eyes, ears, and mouth. In case of contact with eyes, rinse eyes thoroughly with water.

In case of adverse skin reactions

visit a hospital and follow your doctor's instructions.

Directions

- Put 1 tablet of disinfectant in 2 liters of water and wait for 2 minutes.
- Put it in a sprayer and spray an appropriate amount on the area where virus, bacteria, and bacteria need to be sterilized.
- It is recommended to use 1 tablet of disinfectant in an electric sprayer with a capacity of 2L to 3L.

Other information

- Sealed storage lengthens the storage period.
- Avoid direct sunlight and store in a cool dry place.

Inactive ingredients

Sodium chlorite, Sodium sulfite, Citric acid, Maleic acid